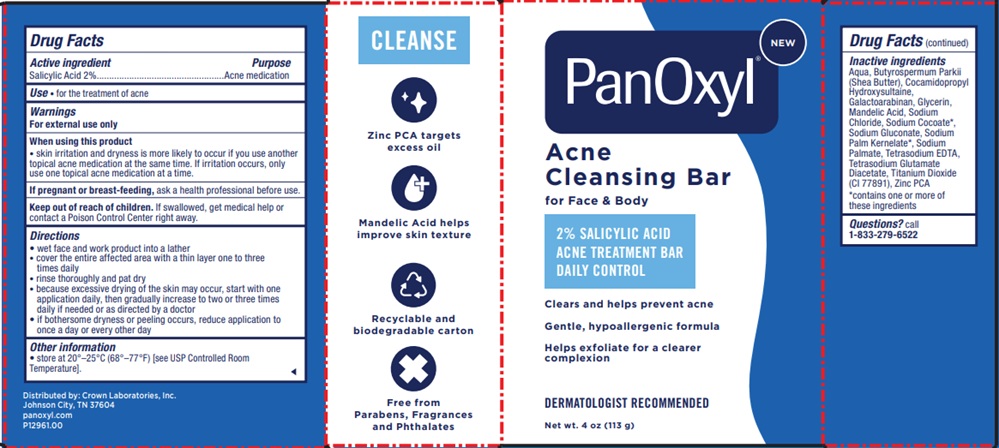 DRUG LABEL: PanOxyl
NDC: 0316-0288 | Form: SOAP
Manufacturer: Crown Laboratories
Category: otc | Type: HUMAN OTC DRUG LABEL
Date: 20260122

ACTIVE INGREDIENTS: SALICYLIC ACID 20 mg/1 g
INACTIVE INGREDIENTS: WATER; GALACTOARABINAN; TETRASODIUM EDTA; TITANIUM DIOXIDE; BUTYROSPERMUM PARKII (SHEA) BUTTER; SODIUM GLUCONATE; ZINC PCA; GLYCERIN; TETRASODIUM GLUTAMATE DIACETATE; SODIUM CHLORIDE; COCAMIDOPROPYL HYDROXYSULTAINE; MANDELIC ACID; SODIUM COCOATE; SODIUM PALM KERNELATE; SODIUM PALMATE

Panoxyl Acne Cleansing Bar

Active ingredient

Salicylic Acid 2%

Purpose

Acne medication

Use

- for the treatment of acne

Warnings

For external use only

When using this product

- skin irritation and dryness is more likely to occur if you use another topical acne medication at the same time. If irritation occurs, only use one topical acne medication at a time.

If pregnant or breast-feeding,

ask a health professional before use.

Keep out of reach of children.

If swallowed, get medical help or contact a Poison Control Center right away.

Directions

- wet face and work product into a lather
- cover the entire affected area with a thin layer one to three times daily
- rinse thoroughly and pat dry
- because excessive drying of the skin may occur, start with one application daily, then gradually increase to two or three times daily if needed or as directed by a doctor
- if bothersome dryness or peeling occurs, reduce application to once a day or every other day

Other information

- Store at 20o- 25oC (68o- 77oF) [see USP Controlled Room Temperature].

Inactive ingredients

Aqua, Butyrospermum Parkii (Shea Butter), Cocamidopropyl Hydroxysultaine, Galactoarabinan, Glycerin, Mandelic Acid, Sodium Chloride, Sodium Cocoate*, Sodium Gluconate, Sodium Palm Kernelate*, Sodium Palmate, Tetrasodium EDTA, Tetrasodium Glutamate Diacetate, Titanium Dioxide (CI 77891), Zinc PCA *contains one or more of these ingredients

Questions?

call 1-833-279-6522

Panoxyl Acne Treatmet Bar Carton

PanOxyl

Acne Cleansing Bar

for Face & Body

2% SALICYLIC ACID

ACNE TREATMENT BAR

DAILY CONTROL

Clears and helps prevent acne

Gentle, hypoallergenic formula

Helps exfoliate for a clearer complexion

DERMATOLOGIST RECOMMENDED

Net wt. 4 oz (113 g)

Distributed by: Crown Laboratories, Inc.

Johnson City, TN 37604

panoxyl.com

P12961.00